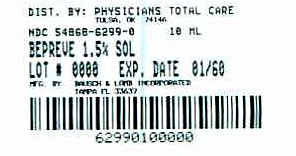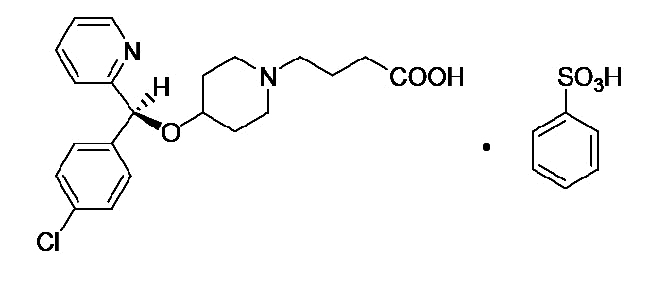 DRUG LABEL: BEPREVE
NDC: 54868-6299 | Form: SOLUTION/ DROPS
Manufacturer: Physicians Total Care, Inc.
Category: prescription | Type: HUMAN PRESCRIPTION DRUG LABEL
Date: 20090801

ACTIVE INGREDIENTS: BEPOTASTINE 15 mg/1 mL
INACTIVE INGREDIENTS: SODIUM PHOSPHATE, MONOBASIC, DIHYDRATE; SODIUM CHLORIDE; SODIUM HYDROXIDE; WATER; BENZALKONIUM CHLORIDE

HIGHLIGHTS OF PRESCRIBING INFORMATION

These highlights do not include all the information needed to use BEPREVE™ (bepotastine besilate ophthalmic solution) 1.5% safely and effectively. See full prescribing information for BEPREVE™.
BEPREVE™ (bepotastine besilate ophthalmic solution) 1.5%
Initial U.S. Approval: 2009

1 INDICATIONS AND USAGE

BEPREVE™ is a histamine H1 receptor antagonist indicated for the treatment of itching associated with allergic conjunctivitis. (1)

2 DOSAGE AND ADMINISTRATION

Instill one drop into the affected eye(s) twice a day (BID). (2)

3 DOSAGE FORMS AND STRENGTHS

Solution containing bepotastine besilate, 1.5%. (3)

5 WARNINGS AND PRECAUTIONS

- To minimize the risk of contamination, do not touch dropper tip to any surface. Keep bottle tightly closed when not in use. (5.1)
- BEPREVE™ should not be used to treat contact lens-related irritation. (5.2)
- Remove contact lenses prior to instillation of BEPREVE™. (5.2)

6 ADVERSE REACTIONS

The most common adverse reaction occurring in approximately 25% of patients was a mild taste following instillation. Other adverse reactions which occurred in 2-5% of subjects were eye irritation, headache, and nasopharyngitis. (6)

To report SUSPECTED ADVERSE REACTIONS, contact ISTA Pharmaceuticals, Inc. at 1-877-788-2020, or FDA at 1-800-FDA-1088 or www.fda.gov/medwatch.

FULL PRESCRIBING INFORMATION

1 INDICATIONS AND USAGE

BEPREVE™ (bepotastine besilate ophthalmic solution) 1.5% is a histamine H1 receptor antagonist indicated for the treatment of itching associated with signs and symptoms of allergic conjunctivitis.

2 DOSAGE AND ADMINISTRATION

Instill one drop of BEPREVE™ into the affected eye(s) twice a day (BID).

3 DOSAGE FORMS AND STRENGTHS

Topical ophthalmic solution containing bepotastine besilate 1.5%.

5 WARNINGS AND PRECAUTIONS

5.1 Contamination of Tip and Solution

To minimize contaminating the dropper tip and solution, care should be taken not to touch the eyelids or surrounding areas with the dropper tip of the bottle. Keep bottle tightly closed when not in use.

5.2 Contact Lens Use

Patients should be advised not to wear a contact lens if their eye is red. BEPREVE™ should not be used to treat contact lens-related irritation.

BEPREVE™ should not be instilled while wearing contact lenses. Remove contact lenses prior to instillation of BEPREVE™. The preservative in BEPREVE™, benzalkonium chloride, may be absorbed by soft contact lenses. Lenses may be reinserted after 10 minutes following administration of BEPREVE™.

5.3 Topical Ophthalmic Use Only

BEPREVE™ is for topical ophthalmic use only.

6 ADVERSE REACTIONS

The most common reported adverse reaction occurring in approximately 25% of subjects was a mild taste following instillation. Other adverse reactions occurring in 2-5% of subjects were eye irritation, headache, and nasopharyngitis.

8 USE IN SPECIFIC POPULATIONS

8.1 Pregnancy

Pregnancy Category C: Teratogenicity studies have been performed in animals. Bepotastine besilate was not found to be teratogenic in rats during organogenesis and fetal development at oral doses up to 200 mg/kg/day (representing a systemic concentration approximately 3,300 times that anticipated for topical ocular use in humans), but did show some potential for causing skeletal abnormalities at 1,000 mg/kg/day. There were no teratogenic effects seen in rabbits at oral doses up to 500 mg/kg/day given during organogenesis and fetal development (>13,000 times the dose in humans on a mg/kg basis). Evidence of infertility was seen in rats given oral bepotastine besilate 1,000 mg/kg/day however, no evidence of infertility was observed in rats given 200 mg/kg/day (approximately 3,300 times the topical ocular use in humans). The concentration of radiolabeled bepotastine besilate was similar in fetal liver and maternal blood plasma following a single 3 mg/kg oral dose. The concentration in other fetal tissues was one-third to one-tenth the concentration in maternal blood plasma.

An increase in stillborns and decreased growth and development were observed in pups born from rats given oral doses of 1,000 mg/kg/day during perinatal and lactation periods. There were no observed effects in rats treated with 100 mg/kg/day.

There are no adequate and well-controlled studies of bepotastine besilate in pregnant women. Because animal reproduction studies are not always predictive of human response, BEPREVE™ (bepotastine besilate ophthalmic solution) 1.5% should be used during pregnancy only if the potential benefit justifies the potential risk to the fetus.

8.3 Nursing Mothers

Following a single 3 mg/kg oral dose of radiolabeled bepotastine besilate to nursing rats 11 days after delivery, the maximum concentration of radioactivity in milk was 0.40 μg eq/mL 1 hour after administration; at 48 hours after administration the concentration was below detection limits. The milk concentration was higher than the maternal blood plasma concentration at each time of measurement.

It is not known if bepotastine besilate is excreted in human milk. Caution should be exercised when BEPREVE™ (bepotastine besilate ophthalmic solution) 1.5% is administered to a nursing woman.

8.4 Pediatric Use

Safety and efficacy of BEPREVE™ (bepotastine besilate ophthalmic solution) 1.5% have not been established in pediatric patients under 2 years of age. Efficacy in pediatric patients under 10 years of age was extrapolated from clinical trials conducted in pediatric patients greater than 10 years of age and from adults.

8.5 Geriatric Use

No overall difference in safety or effectiveness has been observed between elderly and younger patients.

11 DESCRIPTION

BEPREVE™ (bepotastine besilate ophthalmic solution) 1.5% is a sterile, topically administered drug for ophthalmic use. Each mL of BEPREVE™ contains 15 mg bepotastine besilate.

Bepotastine besilate is designated chemically as (+) -4-[[(S)-p-chloro-alpha -2-pyridylbenzyl]oxy]-1-piperidine butyric acid monobenzenesulfonate. The chemical structure for bepotastine besilate is:

Bepotastine besilate is a white or pale yellowish crystalline powder. The molecular weight of bepotastine besilate is 547.06 daltons. BEPREVE™ ophthalmic solution is supplied as a sterile, aqueous 1.5% solution, with a pH of 6.8.

The osmolality of BEPREVE™ (bepotastine besilate ophthalmic solution) 1.5% is approximately 290 mOsm/kg.

Each mL of BEPREVE™ (bepotastine besilate ophthalmic solution) 1.5% contains:

Active: Bepotastine besilate 15 mg (equivalent to 10.7 mg bepotastine)

Preservative: benzalkonium chloride 0.005%

Inactives: monobasic sodium phosphate dihydrate, sodium chloride, sodium hydroxide to adjust pH, and water for injection, USP.

12 CLINICAL PHARMACOLOGY

12.1 Mechanism of Action

Bepotastine is a topically active, direct H1-receptor antagonist and an inhibitor of the release of histamine from mast cells.

12.3 Pharmacokinetics

Absorption: The extent of systemic exposure to bepotastine following topical ophthalmic administration of bepotastine besilate 1% and 1.5% ophthalmic solutions was evaluated in 12 healthy adults. Following one drop of 1% or 1.5% bepotastine besilate ophthalmic solution to both eyes four time daily (QID) for seven days, bepotastine plasma concentrations peaked at approximately one to two hours post-instillation. Maximum plasma concentration for the 1% and 1.5% strengths were 5.1 ± 2.5 ng/mL and 7.3 ± 1.9 ng/mL, respectively. Plasma concentration at 24 hours post-instillation were below the quantifiable limit (2ng/mL) in 11/12 subjects in the two dose groups.

Dtistribution: The extent of protein binding of bepotastine is approximately 55% and independent of bepotastine concentration.

Metabolism: In vitro metabolism studies with human liver microsomes demonstrated that bepotastine is minimally metabolized by CYP450 isozymes.

In vitro studies demonstrated that bepotastine besilate does not inhibit the metabolism of various cytochrome P450 substrate via inhibition of CYP3A4, CYP2C9, and CYP2C19. The effect of bepotastine besilate on the metabolism of substrates of CYP1A2, CYP2C8, CYP2D6 was not studied. Bepotastine besilate has a low potential for drug interaction via inhibition of CYP3A4, CYP2C9, and CYP2C19.

Excretion: The main route of elimination of bepotastine besilate is urinary excretion (with approximately 75-90% excreted unchanged in urine).

13 NONCLINICAL TOXICOLOGY

13.1 Carcinogenesis, Mutagenesis and Impairment of Fertility

Long-term dietary studies in mice and rats were conducted to evaluate the carcinogenic potential of bepotastine besilate. Bepotastine besilate did not significantly induce neoplasms in mice receiving a nominal dose of up to 200 mg/kg/day for 21 months or rats receiving a nominal dose of up to 97 mg/kg/day for 24 months. These dose levels represent systemic exposures approximating 350 and 200 times that achieved with human topical ocular use.

The no observable adverse effect levels for bepotastine besilate based on nominal dose levels in carcinogenicity tests were 18.7 to 19.9 mg/kg/day in mice and 9.6 to 9.8 mg/kg/day in rats (representing exposure margins of approximately 60 and 20 times the systemic exposure anticipated for topical use in humans).

There was no evidence of genotoxicity in the Ames test, in CHO cells (chromosome aberrations), in mouse hepatocytes (unscheduled DNA synthesis), or in the mouse micronucleus test.

When oral bepotastine was administered to male and female rats at doses up to 1,000 mg/kg/day, there was a slight reduction in fertility index and surviving fetuses. Infertility was not seen in rats given 200 mg/kg/day oral bepotastine besilate (approximately 3,300 times the systemic concentration anticipated for topical ocular use in humans).

14 CLINICAL STUDIES

Clinical efficacy was evaluated in 2 conjunctival allergen challenge (CAC) studies (237 patients). BEPREVE™ (bepotastine besilate ophthalmic solution) 1.5% was more effective than its vehicle for relieving ocular itching induced by an ocular allergen challenge, both at a CAC 15 minutes post-dosing and a CAC 8 hours post dosing of BEPREVE™.

The safety of BEPREVE™ was evaluated in a randomized clinical study of 861 subjects over a period of 6 weeks.

16 HOW SUPPLIED/STORAGE AND HANDLING

BEPREVE™ (bepotastine besilate ophthalmic solution) 1.5% is supplied in a white low density polyethylene plastic squeeze bottle with a white controlled dropper tip and a white polypropylene cap in the following size:

10 mL (NDC 54868-6299-0)

STORAGE
Store at 15º – 25ºC (59º – 77ºF).

17 PATIENT COUNSELING INFORMATION

17.1 Topical Ophthalmic Use Only

For topical ophthalmic administration only.

17.2 Sterility of Dropper Tip

Patients should be advised to not touch dropper tip to any surface, as this may contaminate the contents.

17.3 Concomitant Use of Contact Lenses

Patients should be advised not to wear a contact lens if their eye is red. Patients should be advised that BEPREVE™ should not be used to treat contact lens-related irritation.

Patients should also be advised to remove contact lenses prior to instillation of BEPREVE™. The preservative in BEPREVE™, benzalkonium chloride, may be absorbed by soft contact lenses. Lenses may be reinserted after 10 minutes following administration of BEPREVE™.

Manufactured for: ISTA Pharmaceuticals®, Inc.
Irvine, CA 92618
By: Bausch & Lomb Incorporated
Tampa, FL 33637
Under license from:
Senju Pharmaceutical Co., Ltd.
Osaka, Japan 541-004
® and ™ marks owned by ISTA Pharmaceuticals, Inc.
U.S. Patents: 6,307,052; 6,780,877
©2009 ISTA Pharmaceuticals, Inc.

Relabeling of additional barcode by:
Physicians Total Care, Inc.
Tulsa, OK 74146

PRINCIPAL DISPLAY PANEL

BEPREVE™ (bepotastine besilate ophthalmic solution) 1.5%

Sterile 10 mL NDC 54868-6299-0

For topical application in the eye.

Store at 15o-25oC (59o-77oF)

Rx only